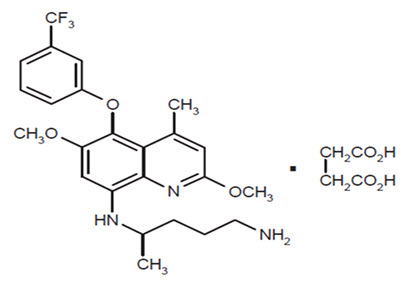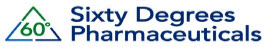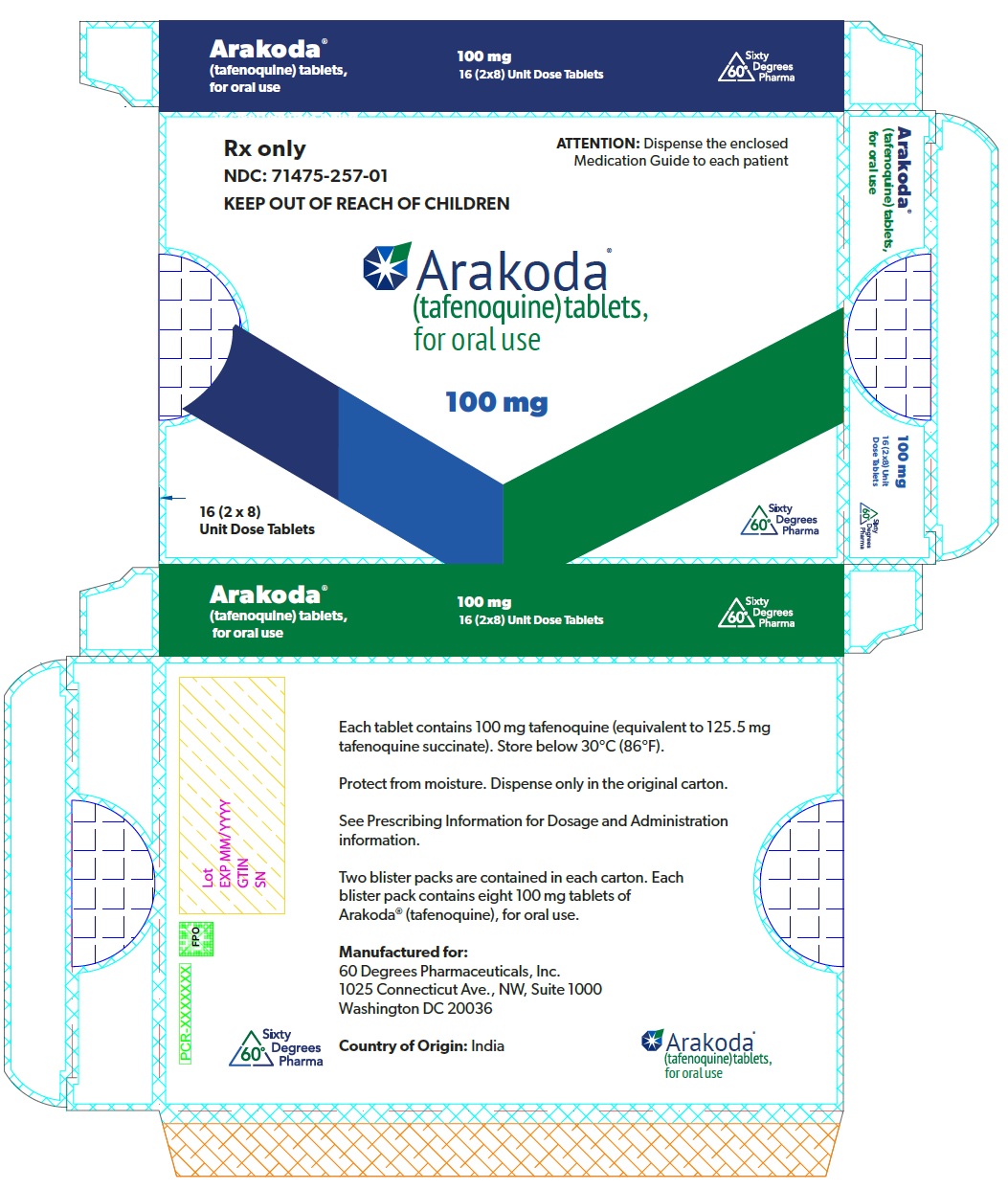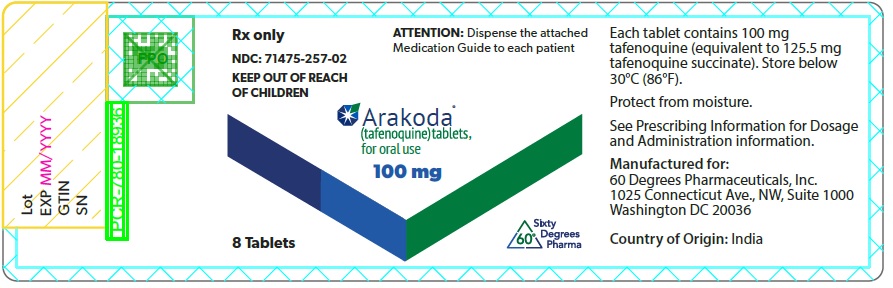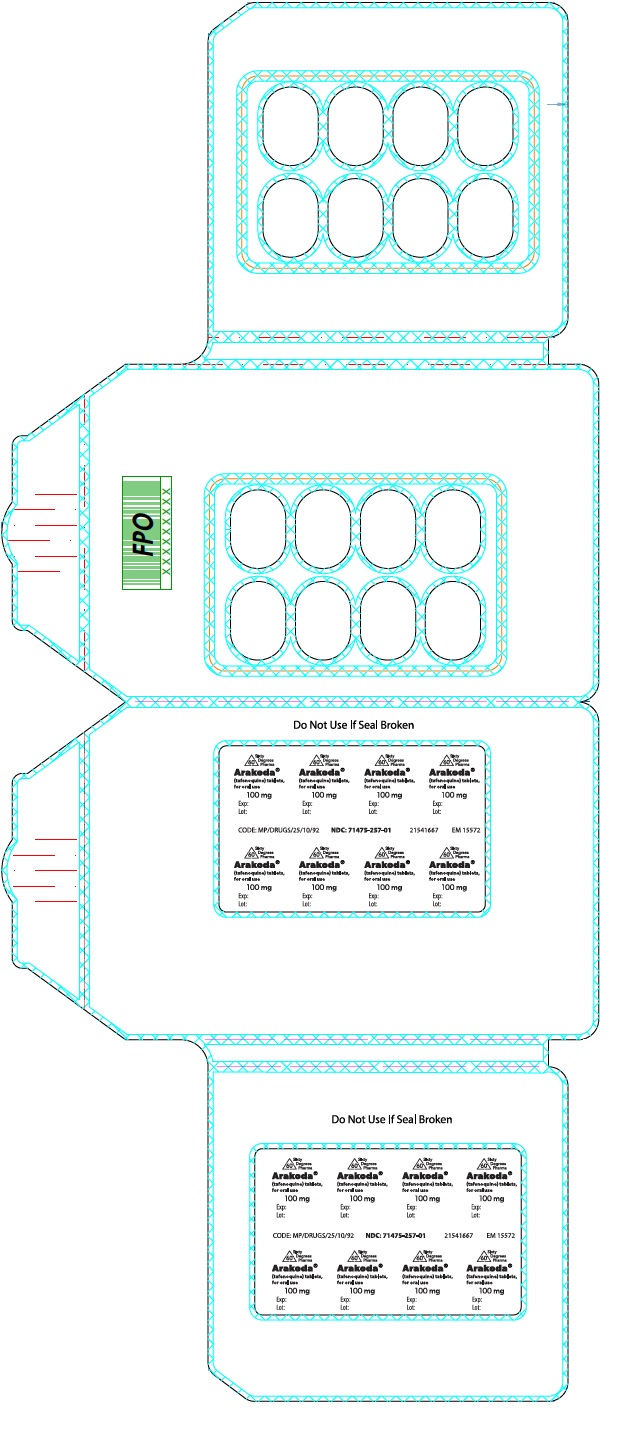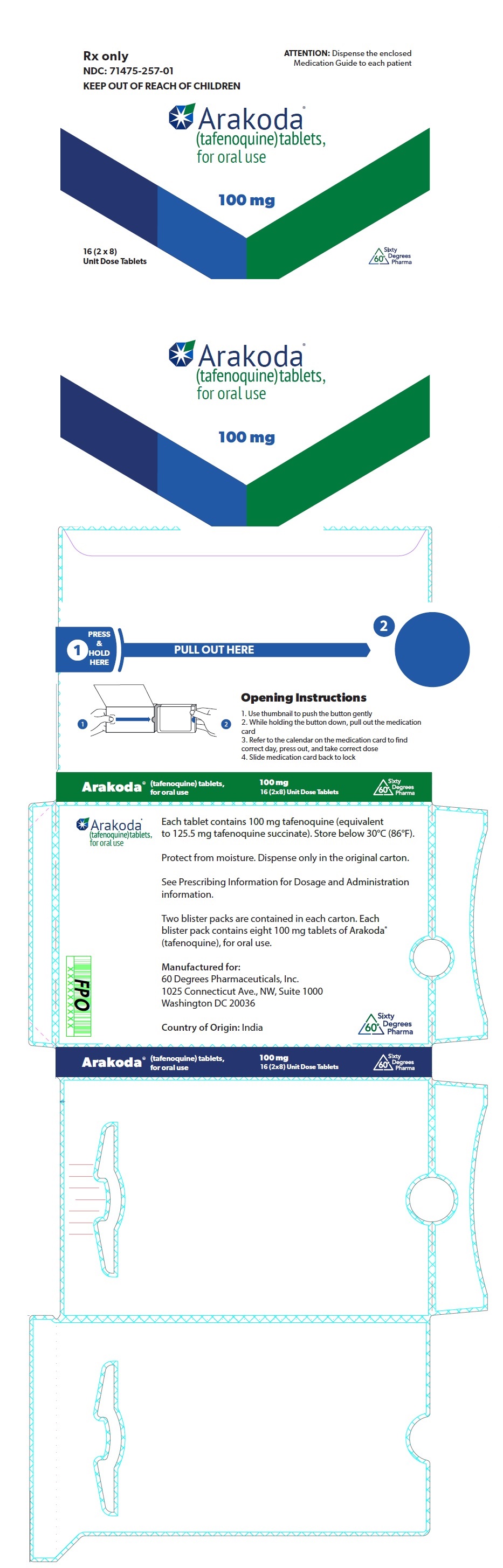 DRUG LABEL: Arakoda
NDC: 71475-257 | Form: TABLET, FILM COATED
Manufacturer: 60 Degrees Pharmaceuticals, INC.
Category: prescription | Type: HUMAN PRESCRIPTION DRUG LABEL
Date: 20250110

ACTIVE INGREDIENTS: TAFENOQUINE 100 mg/1 1
INACTIVE INGREDIENTS: MAGNESIUM STEARATE; MANNITOL; MICROCRYSTALLINE CELLULOSE; HYPROMELLOSE, UNSPECIFIED; FERRIC OXIDE RED; POLYETHYLENE GLYCOL, UNSPECIFIED; TITANIUM DIOXIDE

HIGHLIGHTS OF PRESCRIBING INFORMATION

These highlights do not include all the information needed to use ARAKODA™ safely and effectively. See full prescribing information for ARAKODA™.
ARAKODA™ (tafenoquine) tablets, for oral use
Initial U.S. Approval: 2018

1 INDICATIONS AND USAGE

ARAKODA is an antimalarial indicated for the prophylaxis of malaria in patients aged 18 years and older. (1)

2 DOSAGE AND ADMINISTRATION

- All patients must be tested for glucose-6-phosphate dehydrogenase (G6PD) deficiency prior to prescribing ARAKODA. (2.1)
- Pregnancy testing is recommended for females of reproductive potential prior to initiating treatment with ARAKODA. (2.1)

Regimen Name | Timing | Dosage
Loading regimen | For each of the 3 days before travel to a malarious area | 200 mg (2 of the 100 mg tablets) once daily for 3 days
Maintenance regimen | While in the malarious area | 200 mg (2 of the 100 mg tablets) once weekly – start 7 days after the last loading regimen dose
Terminal prophylaxis regimen | In the week following exit from the malarious area | 200 mg (2 of the 100 mg tablets) one-time 7 days after the last maintenance dose

- Administer ARAKODA with food. (2.2)
- See full prescribing information for instructions on how to replace missed doses. (2.2)

3 DOSAGE FORMS AND STRENGTHS

Tablets: 100 mg of tafenoquine (3)

4 CONTRAINDICATIONS

- G6PD deficiency or unknown G6PD status (4)
- Breastfeeding by a lactating woman when the infant is found to be G6PD deficient or if G6PD status is unknown (4, 8.2)
- Patients with a history of psychotic disorders or current psychotic symptoms (4, 5.4)
- Known hypersensitivity reactions to tafenoquine, other 8-aminoquinolines, or any component of ARAKODA. (4)

5 WARNINGS AND PRECAUTIONS

- Hemolytic Anemia: G6PD testing must be performed before prescribing ARAKODA due to the risk of hemolytic anemia. Monitor patients for signs or symptoms of hemolysis. (5.1)
- G6PD Deficiency in Pregnancy or Lactation: ARAKODA may cause fetal harm when administered to a pregnant woman with a G6PD-deficient fetus. ARAKODA is not recommended during pregnancy. A G6PD-deficient infant may be at risk for hemolytic anemia from exposure to ARAKODA through breast milk. Check infant’s G6PD status before breastfeeding begins. (5.2, 8.1, 8.2)
- Methemoglobinemia: Asymptomatic elevations in blood methemoglobin have been observed. Initiate appropriate therapy if signs or symptoms of methemoglobinemia occur. (5.3)
- Psychiatric Effects: Serious psychotic adverse reactions have been observed in patients with a history of psychosis or schizophrenia, at doses different from the approved dose. If psychotic symptoms (hallucinations, delusions, or grossly disorganized thinking or behavior) occur, consider discontinuation of ARAKODA therapy and, evaluation by a mental health professional as soon as possible. (5.4)
- Hypersensitivity Reactions: Serious hypersensitivity reactions have been observed with administration of ARAKODA. If hypersensitivity reactions occur, institute appropriate therapy. (5.5)
- Delayed Adverse Reactions: Due to the long half-life of ARAKODA (approximately 17 days), psychiatric effects, hemolytic anemia, methemoglobinemia, and hypersensitivity reactions may be delayed in onset and/or duration. (5.6, 12.3)

6 ADVERSE REACTIONS

The most common adverse reactions (incidence ≥1%) were: headache, dizziness, back pain, diarrhea, nausea, vomiting, increased alanine aminotransferase (ALT), motion sickness, insomnia, depression, abnormal dreams, anxiety. (6.1)

To report SUSPECTED ADVERSE REACTIONS, contact 60 Degrees Pharmaceuticals at 1-888-834-0225 or FDA at 1-800-FDA-1088 or www.fda.gov/medwatch.

7 DRUG INTERACTIONS

Avoid co-administration with drugs that are substrates of organic cation transporter-2 (OCT2) or multidrug and toxin extrusion (MATE) transporters (7.1)

8 USE IN SPECIFIC POPULATIONS

Lactation: Advise women not to breastfeed a G6PD-deficient infant or infant with unknown G6PD status during treatment and for 3 months after the last dose of ARAKODA. (5.2, 8.2)

FULL PRESCRIBING INFORMATION

1 INDICATIONS AND USAGE

ARAKODA is indicated for the prophylaxis of malaria in patients aged 18 years and older.

2 DOSAGE AND ADMINISTRATION

2.1 Tests to be Performed Prior to ARAKODA Dose Initiation

All patients must be tested for glucose-6-phosphate dehydrogenase (G6PD) deficiency prior to prescribing ARAKODA [see Contraindications (4), Warnings and Precautions (5.1)].

Pregnancy testing is recommended for females of reproductive potential prior to initiating treatment with ARAKODA [see Use in Specific Populations (8.1 and 8.3)].

2.2 Recommended Dosage and Administration Instructions

The recommended dosage of ARAKODA is described in Table 1 below. ARAKODA can be administered for up to 6 months of continuous dosing.

Table 1: Recommended Dosage of ARAKODA in Patients (18 Years of Age and Older)
Regimen Name | Timing | Dosage
Loading regimen | For each of the 3 days before travel to a malarious area | 200 mg (2 of the 100 mg tablets) once daily for 3 days
Maintenance regimen | While in the malarious area | 200 mg (2 of the 100 mg tablets) once weekly – start 7 days after the last loading regimen dose
Terminal prophylaxis regimen | In the week following exit from the malarious area | 200 mg (2 of the 100 mg tablets) taken one time, 7 days after the last maintenance dose

- Administer ARAKODA with food. [see Clinical Pharmacology (12.3)].
- Swallow the tablet whole. Do not break, crush or chew the tablets.
- Complete the full course of ARAKODA including the loading dose and the terminal dose.

Table 2: How to Replace Missed Doses of ARAKODA
Dose(s) Missed | How to Replace Missed Dose(s):
1 Loading dose | 1 dose of 200 mg (2 of the 100 mg tablets) so that a total of 3 daily loading doses have been taken. Begin maintenance dose 1 week after the last loading dose.
2 Loading doses | 2 doses of 200 mg (2 of the 100 mg tablets) on 2 consecutive days so that a total of 3 daily loading doses have been taken. Begin maintenance dose 1 week after the last loading dose.
1 Maintenance (weekly) dose | 1 dose of 200 mg (2 of the 100 mg tablets) on any day up to the time of the next scheduled weekly dose.
2 Maintenance (weekly) doses | 1 dose of 200 mg (2 of the 100 mg tablets) on any day up to the time of the next scheduled weekly dose.
3 or more Maintenance (weekly) doses | 2 doses of 200 mg (2 of the 100 mg tablets), taken as 200 mg (2 of the 100 mg tablets) once daily for 2 days up to the time of the next weekly dose.
Terminal prophylaxis dose | 1 dose of 200 mg (2 of the 100 mg tablets) as soon as remembered.

3 DOSAGE FORMS AND STRENGTHS

ARAKODA tablets are dark pink, film-coated, capsule-shaped tablets debossed with ‘TQ100’ on one side containing 100 mg of tafenoquine.

4 CONTRAINDICATIONS

ARAKODA is contraindicated in:

- patients with G6PD deficiency or unknown G6PD status due to the risk of hemolytic anemia [see Warnings and Precautions (5.2)].
- breastfeeding by a lactating woman when the infant is found to be G6PD deficient or if the G6PD status of the infant is unknown [see Warnings and Precautions (5.3), Use in Specific Populations (8.2)].
- patients with a history of psychotic disorders or current psychotic symptoms (i.e., hallucinations, delusions, and/or grossly disorganized behavior) [see Warnings and Precautions (5.4)]
- patients with known hypersensitivity reactions to tafenoquine, other 8-aminoquinolines, or any component of ARAKODA [see Warnings and Precautions (5.5)].

5 WARNINGS AND PRECAUTIONS

5.1 Hemolytic Anemia

Due to the risk of hemolytic anemia in patients with G6PD deficiency, G6PD testing must be performed before prescribing ARAKODA [see Contraindications (4)]. Due to the limitations with G6PD tests, physicians need to be aware of residual risk of hemolysis and adequate medical support and follow-up to manage hemolytic risk should be available. Treatment with ARAKODA is contraindicated in patients with G6PD deficiency or unknown G6PD status [see Contraindications (4)]. In clinical trials, declines in hemoglobin levels were reported in some G6PD-normal patients [see Adverse Reactions (6.1)]. Monitor patients for clinical signs or symptoms of hemolysis [see Warnings and Precautions (5.6)]. Advise patients to discontinue ARAKODA and seek medical attention if signs of hemolysis occur.

5.2 G6PD Deficiency in Pregnancy and Lactation

Potential Harm to the Fetus

The use of ARAKODA during pregnancy may cause hemolytic anemia in a G6PD-deficient fetus. Even if a pregnant woman has normal levels of G6PD, the fetus could be G6PD deficient. Advise females of reproductive potential that treatment with ARAKODA during pregnancy is not recommended and to avoid pregnancy or use effective contraception during treatment and for 3 months after the last dose of ARAKODA. If a pregnancy is detected during ARAKODA use, discontinue ARAKODA as soon as possible and switch to an alternative prophylactic drug for malaria during pregnancy [see Use in Specific Populations (8.1 and 8.3)].

Potential Harm to the Breastfeeding Infant

A G6PD-deficient infant may be at risk for hemolytic anemia from exposure to ARAKODA through breast milk. Infant G6PD status should be checked before breastfeeding begins. ARAKODA is contraindicated in breastfeeding women when the infant is found to be G6PD deficient or the G6PD status of the infant is unknown [see Contraindications (4)]. Advise the woman with a G6PD-deficient infant or if the G6PD status of the infant is unknown not to breastfeed during treatment with ARAKODA and for 3 months after the final dose [see Use in Specific Populations (8.2)].

5.3 Methemoglobinemia

Asymptomatic elevations in methemoglobin have been observed in the clinical trials of ARAKODA [see Adverse Reactions (6.1)]. Institute appropriate therapy if signs or symptoms of methemoglobinemia occur [see Warnings and Precautions (5.6)]. Carefully monitor individuals with nicotinamide adenine dinucleotide (NADH)-dependent methemoglobin reductase deficiency. Advise patients to discontinue ARAKODA and seek medical attention if signs of methemoglobinemia occur.

5.4 Psychiatric Effects

In patients receiving ARAKODA in clinical trials, psychiatric adverse reactions included sleep disturbances (2.5%), depression/depressed mood (0.3%), and anxiety (0.2%) [see Adverse Reactions (6.1)]. ARAKODA was discontinued in a subject with an adverse reaction of suicide attempt (0.1%). Subjects with a history of psychiatric disorders were excluded from three of five ARAKODA trials in which mefloquine was included as a comparator.

Psychosis was reported in three patients with a history of psychosis or schizophrenia who received tafenoquine doses (350 mg to 500 mg single dose, or 400 mg daily for 3 days) different from the approved ARAKODA regimen. Safety and effectiveness of ARAKODA have not been established at doses or regimens other than the approved regimen; use of ARAKODA at doses or regimens other than a 200-mg weekly dose is not approved by FDA.

ARAKODA is contraindicated in patients with a history of psychotic disorders or current psychotic symptoms [see Contraindication (4)]. If psychotic symptoms (hallucinations, delusions, or grossly disorganized thinking or behavior) occur, consider discontinuation of ARAKODA and prompt evaluation by a mental health professional as soon as possible. Other psychiatric symptoms, such as changes in mood, anxiety, insomnia, and nightmares, should be promptly evaluated by a medical professional if they are moderate and last more than three days or are severe [see Warnings and Precautions (5.6)].

5.5 Hypersensitivity Reactions

Serious hypersensitivity reactions (e.g., angioedema and urticaria) have been observed with administration of tafenoquine. Hypersensitivity reactions have been reported in clinical trials of ARAKODA [see Adverse Reactions (6.1)]. Discontinue prophylaxis with ARAKODA and institute appropriate therapy if hypersensitivity reactions occur [see Warnings and Precautions (5.6)]. ARAKODA is contraindicated in patients who develop hypersensitivity to tafenoquine or any component of ARAKODA or other 8-aminoquinolines [see Contraindications (4)].

5.6 Delayed Adverse Reactions, Including Hemolytic Anemia, Methemoglobinemia, Psychiatric Effects, and Hypersensitivity Reactions

Adverse reactions including hemolytic anemia, methemoglobinemia, psychiatric effects, and hypersensitivity reactions were reported with the use of ARAKODA or tafenoquine in clinical trials [see Warnings and Precautions (5.1, 5.3, 5.4, 5.5)]. Due to the long half-life of ARAKODA (approximately 17 days), psychiatric effects, hemolytic anemia, methemoglobinemia, and signs or symptoms of hypersensitivity reactions that may occur could be delayed in onset and/or duration. Advise patients to seek medical attention if signs of hypersensitivity occur [see Clinical Pharmacology (12.3)].

6 ADVERSE REACTIONS

The following clinically significant adverse reactions observed with ARAKODA are discussed in detail in the Warnings and Precautions section:

- Hemolytic Anemia [see Warnings and Precautions (5.2)]
- Methemoglobinemia [see Warnings and Precautions (5.3)]
- Psychiatric Effects [see Warnings and Precautions (5.4)]
- Hypersensitivity Reactions [see Warnings and Precautions (5.5)]

6.1 Clinical Trials Experience

Because clinical trials are conducted under widely varying conditions, adverse reaction rates observed in the clinical trials of a drug cannot be directly compared with rates in the clinical trials of another drug and may not reflect the rates observed in practice.

The safety of tafenoquine was studied in clinical trials at various doses and regimens in 3,184 subjects. The recommended ARAKODA regimen was evaluated in 825 subjects in 5 controlled clinical trials (Trials 1, Trial 2, Trial 3, Trial 4 and Trial 5). The mean duration of exposure to ARAKODA in these five clinical trials was 21 weeks (range 10-29 weeks). Trial 1, 2 and 4 were conducted in healthy semi-immune volunteers in Ghana or Kenya and were placebo-controlled; a mefloquine arm was included in Trials 2 and 4 as a benchmark. Trial 3, an active comparator (mefloquine) controlled trial was conducted in healthy soldiers deployed in East Timor (Timor Leste). A placebo-controlled Trial 5 was conducted in healthy volunteers in the United States and United Kingdom. The mean age of the subjects included in the five trials was 29 years (range 17 to 69 years); 84% were male.

Adverse Reactions Reported with ARAKODA in Trial 3 and Pooled Trials 1, 2, 4, and 5

Adverse reactions occurring in ≥1% of subjects in the ARAKODA group in the placebo-controlled pooled Trials 1, 2, 3, and 4 are presented in Table 3.

Table 3: Selected Adverse Reactions Occurring in ≥1% of Subjects Receiving ARAKODA in Pooled Trials 1, 2, 4, and 5 (Non-Deployed Subjects)
Adverse Reaction | ARAKODA^1 (n=333) % | Placebo (n=295) % | Mefloquine^2 (n=147) %
Nervous system Disorders | 35 | 34 | 47
Headache^3 | 32 | 32 | 44
Dizziness^4 | 5 | 3 | 10
Musculoskeletal and connective tissue disorders | 27 | 26 | 37
Back pain | 14 | 9 | 11
Gastrointestinal disorders | 31 | 33 | 46
Diarrhea | 5 | 3 | 1
Nausea | 5 | 2 | 2
Vomiting | 2 | 2 | 1
Investigations | 8 | 7 | 11
Alanine Aminotransferase (ALT) increased/abnormal | 4 | 2 | 3
Psychiatric disorders | 2 | 1 | 2
Any sleep symptom^5 | 1 | 1 | 0
Insomnia | 1 | 1 | 0
Depression/depressed mood | 1 | 0 | 0
^1 ARAKODA was administered as 200 mg daily for 3 days, then 200 mg weekly
^2 Mefloquine was administered as 250 mg daily for 3 days, then 250 mg weekly
^3 Includes headache, sinus headache, migraine and tension headache.
^4 Includes dizziness and dizziness postural
^5 Includes abnormal dreams, insomnia, nightmares, sleep disorder, and somnambulism.

Adverse reactions occurring in ≥1% of subjects in the ARAKODA group in the active-control Trial 3 conducted in military personnel deployed to malaria endemic areas are presented in Table 4.

Table 4: Selected Adverse Reactions Occurring in ≥1% of Subjects Receiving ARAKODA in Trial 3 (Deployed Subjects)
Adverse Reaction | ARAKODA^1 (n=492) % | Mefloquine^2 (n=162) %
Nervous system Disorders | 22 | 27
Headache^3 | 15 | 19
Dizziness^4 | 1 | 1
Ear and labyrinth Disorders | 7 | 11
Motion sicknesss^5 | 5 | 6
Musculoskeletal and connective tissue disorders | 29 | 30
Back pain | 14 | 15
Gastrointestinal disorders | 36 | 41
Diarrhea | 18 | 20
Nausea | 7 | 9
Vomiting | 5 | 6
Psychiatric disorders | 5 | 4
Any sleep symptom^6 | 4 | 4
Insomnia | 2 | 1
Abnormal dreams^7 | 2 | 2
Anxiety^8 | 1 | 0
^1 ARAKODA was administered as 200 mg daily for 3 days, then 200 mg weekly
^2 Mefloquine was administered as 250 mg daily for 3 days, then 250 mg weekly
^3 Includes headache, sinus headache, migraine and tension headache.
^4 Includes dizziness and dizziness postural
^5 Includes motion sickness, vertigo and vertigo positional.
^6 Includes abnormal dreams, insomnia, nightmares, sleep disorder, and somnambulism.
^7 Includes abnormal dreams, nightmares
^8 Includes anxiety disorder, panic attack and stress.

Clinically Significant Adverse Reactions in Trials 1 to 5 (Overall Safety Population)

Clinically significant adverse reactions with ARAKODA (200 mg daily for 3 days, followed by 200 mg weekly) in Trials 1 to 5 (n= 825) are described below:

Ocular Adverse Reactions

Vortex keratopathy was reported in 21% to 93% of subjects receiving ARAKODA in the trials which included ophthalmic evaluations (Trials 3, 5, and Trial 6 (NCT # 01290601, an active-control trial in patients from Thailand with P. vivax malaria. The keratopathy did not result in any apparent functional visual changes and resolved within one year after drug cessation in all patients. Retinal abnormalities were noted in less than 1% of subjects receiving ARAKODA.

A total of 7 serious ocular adverse reactions (SARs) were reported in ARAKODA-treated subjects in the trials which included ophthalmic evaluations: 5 reports of keratopathy and two reports of retinal disorders.

Laboratory Abnormalities

Methemoglobinemia: Asymptomatic methemoglobin elevations were observed in 13% of subjects receiving ARAKODA.

Hemoglobin decrease: Hemoglobin decreases of ≥ 3 g/dL were observed in 2.3% of subjects receiving ARAKODA.

Adverse Reactions Reported in < 1% of Subjects Receiving ARAKODA in Trials 1 to 5

The following selected adverse reactions were reported in subjects receiving ARAKODA in Trials 1 to 5 at a rate of less than 1%.

Blood and lymphatic system disorders: hemolytic anemia, anemia, thrombocytopenia

Ear and labyrinth disorders: hyperacusis, Meniere’s disease

Eye disorders: night blindness, photophobia, blurred vision, visual acuity reduced, visual impairment, vitreous floaters

Hepatobiliary disorders: hyperbilirubinemia, jaundice cholestatic

Immune system disorders: hypersensitivity

Investigations: blood bilirubin increased, blood creatinine increased, glomerular filtration rate decreased

Nervous system disorders: amnesia, coordination abnormal, hyperesthesia, hypoesthesia, somnolence, syncope, tremor, visual field defect

Psychiatric disorders: agitation, neurosis

Skin and subcutaneous tissue disorders: urticaria.

7 DRUG INTERACTIONS

7.1 Effect of ARAKODA on Organic Cation Transporter-2 (OCT2) and Multidrug and Toxin Extrusion (MATE) Substrates

The effect of coadministration of tafenoquine on the pharmacokinetics of OCT2 and MATE substrates in humans is unknown. However, in vitro observations suggest the potential for increased concentrations of these substrates [see Clinical Pharmacology (12.3)] which may increase the risk of toxicity of these drugs.

Avoid coadministration of ARAKODA with OCT2 and MATE substrates (e.g., dofetilide, metformin). If coadministration cannot be avoided, monitor for drug-related toxicities and consider dosage reduction if needed based on approved product labeling of the coadministered drug.

8 USE IN SPECIFIC POPULATIONS

8.1 Pregnancy

Risk Summary

The use of ARAKODA during pregnancy may cause hemolytic anemia in a fetus who is G6PD-deficient. Treatment with ARAKODA during pregnancy is not recommended. If a pregnancy is detected during ARAKODA use, discontinue ARAKODA as soon as possible and switch to an alternative prophylactic drug for malaria during pregnancy [see Warnings and Precautions (5.2)]. Available data with use of ARAKODA in pregnant women are insufficient to establish a drug-associated risk of major birth defects, miscarriage or adverse maternal or fetal outcomes. In animal studies, there were increased abortions, with and without maternal toxicity when tafenoquine was given orally to pregnant rabbits at and above doses equivalent to about 0.4 times the clinical exposure based on body surface area comparisons. No fetotoxicity was observed at doses about 1.5 times the clinical exposure (based on body surface area comparisons) in a similar study in rats.

The estimated background risk of major birth defects and miscarriage for the indicated population is unknown. All pregnancies have a background risk of birth defect, loss, or other adverse outcomes. In the U.S. general population, the estimated background risk of major birth defects and miscarriage in clinically recognized pregnancies is 2% to 4% and 15% to 20%, respectively.

Clinical Considerations

Disease-Associated Maternal and/or Embryo/Fetal Risk:

Malaria during pregnancy increases the risk for adverse pregnancy outcomes, including maternal anemia, prematurity, spontaneous abortion and stillbirth.

Data

Animal Data:

Tafenoquine resulted in dose-related abortions when given orally to pregnant rabbits during organogenesis (Gestation Days 6 to 18), at doses of 7 mg/kg (about 0.4 times the clinical exposure based on body surface area comparisons) and above. Doses higher than 7 mg/kg were also associated with maternal toxicity (mortality and reduced body weight gain). In a similar study in rats, doses of 3, 10, or 30 mg/kg/day resulted in maternal toxicity (enlarged spleen, reduced body weight and reduced food intake) but no fetotoxicity at the high dose (about 1.5 times the clinical exposure based on body surface area comparisons). There was no evidence of malformations in either species. In a pre- and postnatal development study in rats, tafenoquine administered throughout pregnancy and lactation produced maternal toxicity and a reversible decrease in offspring body weight gain and decrease in motor activity at 18 mg/kg/day, which is equivalent to about 0.6 times the clinical dose based on body surface area comparisons.

8.2 Lactation

Risk Summary

A breastfed infant with G6PD deficiency is at risk for hemolytic anemia from exposure to ARAKODA. Infant G6PD status should be checked before breastfeeding begins. ARAKODA is contraindicated in breastfeeding women when the infant is found to be G6PD deficient or the G6PD status of the infant is unknown [see Contraindications (4) and Clinical Considerations].

There is no information regarding the presence of ARAKODA in human milk, the effects of the drug on the breastfed infant, or the effects of the drug on milk production. In a breastfed infant with normal G6PD, the developmental and health benefits of breastfeeding should be considered along with the mother’s clinical need for ARAKODA and any potential effects on the breastfed infant from ARAKODA or from the underlying maternal condition.

Clinical Considerations

Check the infant’s G6PD status before maternal breastfeeding commences. If an infant is G6PD-deficient, exposure to ARAKODA during breastfeeding may result in hemolytic anemia in the infant; therefore, advise the woman with an infant who has G6PD deficiency or whose G6PD status is unknown, not to breastfeed during treatment with ARAKODA and for 3 months after the final dose of ARAKODA.

8.3 Females and Males of Reproductive Potential

Pregnancy Testing

Verify the pregnancy status in females of reproductive potential prior to initiating treatment with ARAKODA. [see Dosage and Administration (2.2), Warnings and Precautions, (5.2), and Use in Specific Populations (8.1)].

Contraception

ARAKODA may cause hemolytic anemia in a G6PD-deficient fetus [see Warnings and Precautions (5.2), Use in Specific Populations (8.1)]. Advise females of reproductive potential that treatment with ARAKODA during pregnancy is not recommended and to avoid pregnancy or use effective contraception for 3 months after the final dose of ARAKODA.

8.4 Pediatric Use

Safety and effectiveness of ARAKODA in pediatric patients have not been established.

8.5 Geriatric Use

Clinical trials of ARAKODA did not include sufficient numbers of patients aged 65 years and older to determine whether they respond differently from younger patients. Other reported clinical experience has not identified differences in responses between the elderly and younger patients [see Clinical Pharmacology (12.3)].

8.6 Renal Impairment

The pharmacokinetics of ARAKODA have not been studied in patients with renal impairment. If ARAKODA is administered to such patients, monitoring for adverse reactions associated with ARAKODA is needed [see Warnings and Precautions (5), Adverse Reactions (6)].

8.7 Hepatic Impairment

The pharmacokinetics of ARAKODA have not been studied in patients with hepatic impairment. If ARAKODA is administered to such patients, monitoring for adverse reactions associated with ARAKODA is needed [see Warnings and Precautions (5), Adverse Reactions (6)].

10 OVERDOSAGE

There were no reported cases of ARAKODA overdose. Hemoglobin decline and methemoglobinemia may be encountered in an overdose with ARAKODA. Treatment of overdosage consists of institution of appropriate symptomatic and/or supportive therapy.

11 DESCRIPTION

ARAKODA contains tafenoquine succinate, an antimalarial agent for oral administration. The structural formula of tafenoquine succinate is:

Figure 1: Tafenoquine Succinate Structure

The chemical name of tafenoquine succinate is (±)-8-[(4-amino-1-methylbutyl) amino]-2,6-dimethoxy-4-methyl-5-[3-(trifluoromethyl) phenoxy]quinoline succinate. The molecular formula of tafenoquine succinate is C24H28F3N3O3∙C4H6O4 and its molecular weight is 581.6 as the succinate salt (463.49 as free base).

Each ARAKODA tablet contains 100 mg of tafenoquine (equivalent to 125.5 mg of tafenoquine succinate). Inactive ingredients include magnesium stearate, mannitol, and microcrystalline cellulose. The tablet film coating inactive ingredients include: hypromellose, iron oxide red, macrogol/polyethylene glycol and titanium dioxide.

12 CLINICAL PHARMACOLOGY

12.1 Mechanism of Action

Tafenoquine is an 8-aminoquinoline antimalarial drug [see Microbiology (12.4)].

12.2 Pharmacodynamics

Cardiac Electrophysiology

The effect of tafenoquine on the QT interval was evaluated in a study of healthy adult subjects. In this study, subjects received once daily 400 mg (2 times the approved recommended dosage) doses of tafenoquine for 3 days. The results suggest that the mean increase in the QTcF interval for tafenoquine is less than 20 msec.

12.3 Pharmacokinetics

Absorption

A food effect study was not conducted with the 100 mg ARAKODA tablet. In majority of the clinical trials, tafenoquine was administered under fed conditions. Table 5 provides the pharmacokinetics of tafenoquine following single dose administration of 200 mg ARAKODA (two 100-mg ARAKODA tablets) in 65 healthy adult subjects under fed conditions. In this study, ARAKODA was administered with a high-calorie, high-fat meal (approximately 1000 calories with 19% protein, 31% carbohydrate, and 50% fat).

Table 5. Mean (%CV) Pharmacokinetic Parameters of Tafenoquine Following Single Oral Administration of Two 100-mg ARAKODA Tablets Under Fed Conditions in Healthy Adult Subjects (N=65)
Parameter | Value
Cmax | 147 ng/mL (20.7%)a
Tmax | 14 hr (6 – 72 hr)b
AUCinf | 70 hr*mcg/mL (24.6%)a, c
a Coefficient of Variance (CV)
b Median and (Range)
c Plasma tafenoquine AUCinf increased by 41% when tafenoquine was administered as an investigational capsule formulation with a high-calorie, high-fat meal compared with the fasted state.

Following administration of a single dose of tafenoquine orally under fasted conditions in healthy adult subjects, AUC and Cmax increased dose proportionally over the dose range from 100 mg to 400 mg. When healthy adult subjects received once-weekly administrations of 200 mg tafenoquine orally for ten weeks without a loading dose under fasting conditions, the mean plasma accumulation ratio of tafenoquine was approximately 4.4.

Distribution

Tafenoquine is greater than 99.5% bound to protein in humans. The apparent volume of distribution of tafenoquine in healthy adult subjects is 2470 L [Inter-Individual Variability (IIV): 24.1 %].

Elimination

The apparent oral clearance of tafenoquine is approximately 4.2 L/hr (IIV: 23.6 %) in healthy adult subjects. The mean terminal half-life following administration of ARAKODA is approximately 16.5 days (range: 10.8 days to 27.3 days) in healthy adult subjects.

Metabolism

Negligible metabolism of tafenoquine was observed in vitro in human liver microsomes and hepatocytes. Following administration of tafenoquine orally, once daily for three days to healthy adult subjects, unchanged tafenoquine represented the only notable drug-related component in plasma at approximately 3 days following the first dose of tafenoquine.

Excretion

The full excretion profile of tafenoquine in humans is unknown.

Specific Populations

The pharmacokinetics of tafenoquine were not significantly impacted by age, sex, ethnicity, and body weight. The effect of renal or hepatic impairment on tafenoquine pharmacokinetics is unknown.

Drug Interaction Studies

Clinical Studies

No clinically significant effects on the pharmacokinetics of substrates of cytochrome P450 isoenzymes (CYP)1A2 (caffeine), CYP2D6 (desipramine), CYP2C9 (flurbiprofen), or CYP3A4 (midazolam) were observed following coadministration with tafenoquine in healthy adult subjects.

In Vitro Studies Where Drug Interaction Potential Was Not Further Evaluated Clinically

Tafenoquine inhibited metformin transport via human OCT2, MATE1 and MATE2-K transporters [see Drug Interactions (7)].

Tafenoquine is not an inhibitor of human breast cancer resistance protein (BCRP), P-glycoprotein (P-gp), Organic anion transporter 1/3 (OAT1 or OAT3), Organic anion transporting polypeptide 1B1/1B3 (OATP1B1 or OATP1B3) mediated transport at clinically relevant concentrations. Tafenoquine is also not a substrate of human OATP1B1 or OATP1B3 at clinically relevant concentrations. It is inconclusive as to whether tafenoquine is a substrate of P-gp and/or BCRP mediated transport.

12.4 Microbiology

Mechanism of Action

Tafenoquine, an 8-aminoquinoline antimalarial, is active against all the stages of Plasmodium species that include the hypnozoite (dormant stage) in the liver. Studies in vitro with the erythrocytic forms of Plasmodium falciparum suggest that tafenoquine may exert its effect by inhibiting hematin polymerization and inducing apoptotic like death of the parasite. In addition to its effect on the parasite, tafenoquine causes red blood cell shrinkage in vitro. The molecular target of tafenoquine is not known.

Antimicrobial activity

Tafenoquine is active against pre-erythrocytic (liver) and erythrocytic (asexual) forms as well as gametocytes of Plasmodium species that include P. falciparum and P. vivax. The activity of tafenoquine against the pre-erythrocytic liver stages of the parasite, prevents the development of the erythrocytic forms of the parasite [see Clinical Studies (14)].

Resistance

A potential for development of resistance of Plasmodium species to tafenoquine was not evaluated.

Studies with the erythrocytic forms of P. falciparum strains/isolates suggest a potential for cross-resistance with primaquine, an 8-aminoquinoline. Clinical relevance of such findings is not known.

13 NONCLINICAL TOXICOLOGY

13.1 Carcinogenesis, Mutagenesis, Impairment of Fertility

Carcinogenesis

Two-year oral carcinogenicity studies were conducted in rats and mice. Renal cell adenomas and carcinomas were increased in male rats at doses 1 mg/kg/day and above (0.5 times the clinical exposure based on AUC comparisons). Tafenoquine was not carcinogenic in mice. The relevance of these findings to a carcinogenic risk in humans is unclear.

Mutagenesis

Tafenoquine did not cause mutations or chromosomal damage in 2 definitive in vitro tests (bacterial mutation assay and mouse lymphoma L5178Y cell assay) or in an in vivo oral rat micronucleus test.

Impairment of Fertility

In a rat fertility study, tafenoquine was given orally at 1.5, 5, and 15 mg/kg/day (up to about 0.5 times the human dose based on body surface area comparisons) to males for at least 67 days, including 29 days prior to mating, and to females from 15 days prior to mating through early pregnancy. Tafenoquine resulted in reduced number of viable fetuses, implantation sites, and corpora lutea at 15 mg/kg in the presence of maternal toxicity (mortality, piloerection, rough coat, and reduced body weight).

14 CLINICAL STUDIES

Clinical Trials 1, 2, and 3

Three double-blind, randomized, controlled studies have been performed to evaluate the efficacy of ARAKODA.

Trial 1 (NCT #02491606) was a Phase IIb, placebo-controlled study conducted in Kenya, an area of holoendemic P. falciparum malaria. After taking a three-day presumptive course of halofantrine to eliminate any existing parasitemia, subjects were randomized into one of four groups (placebo and three different ARAKODA dosing groups; one group received 200 mg once daily for 3 days, then a maintenance regimen of weekly dose of 200 mg for 10-15 weeks). Sixty-one percent of subjects were male. The mean age was 32.4 years (range 17-55). Subjects were evaluated for parasitemia by weekly blood smears. Protective efficacy at 15 weeks was defined based on the reduced incidence of parasitemia during the prophylaxis phase relative to placebo. The results in the intention-to-treat population, which included all subjects who received three doses of halofantrine and were randomized, are shown in Table 6 below.

Table 6: Incidence of Parasitemia and Protective Efficacy of ARAKODA at 15 weeks for Trial 1
 | Placebo | ARAKODA^1
Number of subjects | 62 | 61
Subjects free of parasitemia | 5 (8.1%) | 46 (75.4)
Subjects with parasitemia | 54 (87.1%) | 7 (11.5%)
Subjects with missing data | 3 (4.8%) | 8 (13.1%)
Protective efficacy [98.3% CI]^2 | – | 73.3% [54.0%, 84.5%]
^1 200 mg once daily for 3 days, then 200 mg weekly for 10-15 weeks
^2 Protective efficacy is reduced incidence of parasitemia relative to placebo (0: no protection; 1: full protection); CI: confidence interval. Bonferroni adjustment was used for multiple comparisons. Missing outcome was considered a failure due to parasitemia for this analysis.

Trial 2 (NCT #02488902) was a comparison of tafenoquine to placebo for prophylaxis in healthy semi-immune residents of a malarious region in Ghana. After treating existing parasitemia with quinine/doxycycline/primaquine, subjects were randomized into prophylactic groups including ARAKODA and placebo. Patients were administered a loading regimen of daily drug or placebo for 3 days followed by a maintenance regimen of weekly drug or placebo for 12 weeks. For the ARAKODA and placebo groups, males were 65% of the total population. The mean age was 38.4 years and 53.5 years for males and females, respectively, as women in reproductive ages were excluded from the study. The mean weight was 55.4 kg and 47.5 kg for males and females, respectively. Subjects were evaluated for parasitemia by weekly blood smears. Parasitemia required a blood smear positive for asexual stage of P. falciparum. The incidence of parasitemia at week 12 for all randomized subjects who received at least one dose of ARAKODA or placebo is presented in Table 7 below.

Table 7: Incidence of Parasitemia and Protective Efficacy of ARAKODA at Week 12 for Trial 2
 | Placebo | ARAKODA^1
Number of subjects | 94 | 93
Subjects free of parasitemia | 6 (6.4%) | 68 (73.1%)
Subjects with parasitemia | 86 (91.5%) | 12 (12.9%)
Subjects with missing data | 2 (2.1%) | 13 (14.0%)
Protective efficacy [98.75% CI]^2 | – | 71.3% [55.8%, 81.4%]
^1 200 mg once daily for 3 days, then 200 mg weekly for 12 weeks
^2 Protective efficacy is reduced incidence of parasitemia relative to placebo; CI: confidence interval. Bonferroni adjustment was used for multiple comparisons. Missing outcome was considered a failure due to parasitemia for this analysis.

Trial 3 compared ARAKODA with mefloquine for the prophylaxis of both P. falciparum and P. vivax malaria in healthy non-immune soldiers deployed to East Timor (now Timor-Leste). No subject developed malaria during the 26-week prophylactic phase. Subjects were exposed to P. vivax and there is a high likelihood that the study subjects were also exposed to P. falciparum. Since the precise degree of exposure to malaria in study subjects is unknown, this study provides only supportive evidence of efficacy.

Clinical Trial 7

In a randomized, double-blind, placebo-controlled trial (Trial 7) in healthy, non-immune volunteers, ARAKODA was shown to have prophylactic activity directed against blood-stage P. falciparum parasites. Twelve subjects received ARAKODA (200 mg once daily for 3 days, then 200 mg on 10 day) and 4 subjects received placebo. On Day 13, subjects were inoculated with erythrocytes containing viable P. falciparum parasites. Fifteen subjects (93.8%) were of white race. The mean age was 27.5 years (range 20-42). The mean body weight was 72.3 kg (range 56-97.7). The efficacy endpoint was parasitemia by Day 34; parasitemia was based on detection of P. falciparum 18S ribosomal DNA by real time polymerase chain reaction assay (PCR). There was a statistically significant difference in malaria incidence between the two groups; 4/4 (100%) subjects in the placebo group had detectable parasites from Day 17 compared to 0/12 (0%) subjects on ARAKODA were PCR negative at all visits (p<0.0005).

16 HOW SUPPLIED/STORAGE AND HANDLING

How Supplied

ARAKODA tablets contain 100 mg of tafenoquine (equivalent to 125.5 mg of tafenoquine succinate) and are dark pink, film-coated, capsule-shaped, and debossed with ‘TQ100’ on one side.

ARAKODA tablets are packed in blister packs or bottles.

For the blister pack presentation, ARAKODA tablets are packed in polyamide aluminum and PVC formable laminate backed blisters with a polyethylene terephthalate aluminum foil cover. Each blister card contains 8 tablets. Each package contains 2 blister cards (16 tablets) housed in a contiguous outer paperboard child-resistant carton component (NDC 71475-257-01).

For the bottle presentation, ARAKODA tablets are packed in 40 cc, 33 mm white high-density polyethylene bottles with a 33 mm polypropylene screw-top child resistant cap with an induction seal liner. Each bottle contains 8 tablets (NDC 71475-257-02).

Storage

Store at less than 30°C (86°F). Protect from moisture. Dispense only in the original carton or bottle.

17 PATIENT COUNSELING INFORMATION

Advise the patient to read the FDA-approved patient labeling (Medication Guide).

G6PD Testing and Hemolytic Anemia

Inform patients of the need for testing for G6PD deficiency before starting ARAKODA. Advise patients on the symptoms of hemolytic anemia and instruct them to seek medical advice promptly if such symptoms occur. Patients should contact their health care provider if they have darker lips or urine as these may be signs of hemolysis or methemoglobinemia [see Warnings and Precautions (5.1)].

Important Administration Instructions

- Advise patients to take ARAKODA with food.
- Advise patients to swallow the tablet whole and not to break, crush or chew it.
- Advise patients to complete the full course of ARAKODA including the loading dose, maintenance dose and terminal dose.

Potential Harm to the Fetus

Advise females of reproductive potential of the potential risk of ARAKODA to a fetus and to inform their healthcare provider of a known or suspected pregnancy [see Warnings and Precautions (5.2) and Use in Specific Populations (8.1)].

Advise females of reproductive potential to avoid pregnancy or use effective contraception during treatment with ARAKODA and for 3 months after the final dose [see Use in Specific Populations (8.3)].

Lactation

Advise women with a G6PD-deficient infant, or if they do not know the G6PD status of their infant, not to breastfeed during treatment with ARAKODA and for 3 months after the final dose [see Contraindication (4), Warnings and Precautions (5.2), Use in Specific Populations (8.2)].

Methemoglobinemia

Inform patients that methemoglobinemia has occurred with ARAKODA. Advise patients on the symptoms of methemoglobinemia and instruct them to seek medical advice promptly if such symptoms occur [see Warnings and Precautions (5.3)].

Psychiatric Symptoms

Advise patients who experience hallucinations, delusions, or confused thinking while taking ARAKODA to seek medical attention as soon as possible. Other psychiatric symptoms, such as changes in mood, anxiety, insomnia, and nightmares, should be promptly evaluated by a medical professional if they last more than three days or severe [see Warnings and Precautions (5.4)].

Hypersensitivity Reactions

Inform patients that hypersensitivity reactions have occurred with ARAKODA. Advise patients on the symptoms of hypersensitivity reactions and instruct them to seek medical advice promptly if such symptoms occur [see Warnings and Precautions (5.5)].

Manufactured For:
60 Degrees Pharmaceuticals INC,
1025 Connecticut Avenue NW, Suite 1000,
Washington DC 20036

1217a

Medication Guide

ARAKODA (AIR-uh-KOH-duh)
(tafenoquine)
tablets, for oral use

What is the most important information I should know about ARAKODA?

ARAKODA can cause serious side effects including:

- Breakdown of red blood cells (hemolytic anemia). See “Do not take ARAKODA if you:”
  ARAKODA can cause a breakdown of red blood cells (hemolysis) in people with glucose-6-phosphate dehydrogenase (G6PD) deficiency. Your healthcare provider will test you for G6PD deficiency before you start taking ARAKODA. Signs of hemolytic anemia may not happen right away (delayed reaction).Tell your healthcare provider or get emergency medical help right away if you develop signs of hemolytic anemia which include darkening of the urine, dizziness, confusion, feeling tired, light-headedness, or shortness of breath, pale skin or yellowing of the skin and whites of the eyes.
- Decrease of oxygen in your blood caused by a certain type of abnormal red blood cell (methemoglobinemia). Signs and symptoms of methemoglobinemia may not happen right away (delayed reaction). Get medical help right away if you have bluish coloring of the lips or skin, headache, fatigue, shortness of breath, or lack of energy.
- Mental health (psychiatric) symptoms. See “Do not take ARAKODA if you:”
  Sleep problems, depression, anxiety and psychosis have happened while taking ARAKODA. Psychiatric symptoms may not happen right away (delayed reaction). Get emergency medical help right away if you develop hallucinations (seeing or hearing things that are really not there), delusions (false or strange thoughts or beliefs), or if you get confused or have problems thinking while taking ARAKODA. Call your healthcare provider if you develop changes in your mood, anxiety, trouble sleeping (insomnia), or nightmares for 3 days or longer while taking ARAKODA.
- ARAKODA can have other serious side effects. See “What are the possible side effects of ARAKODA?”

What is ARAKODA?

- ARAKODA is a prescription medicine used to help prevent malaria in people 18 years of age and older.
- Malaria is a serious disease of the blood that is spread by infected mosquitos.
- It is not known if ARAKODA is safe and effective in children.

Do not take ARAKODA if you:

- have G6PD deficiency.
- are breastfeeding a child known to have G6PD deficiency or breastfeeding a child that has not been tested for G6PD deficiency.
- have a history of psychotic disorders, or you currently have psychotic symptoms including hallucinations (seeing or hearing things that are not really there), delusions (false or strange thoughts or beliefs), or disorganized thinking or behavior.
- are allergic to tafenoquine, other 8-aminoquinolines, or any of the ingredients in ARAKODA. See the end of this Medication Guide for a complete list of ingredients in ARAKODA.

Before taking ARAKODA, tell your health care provider about all your medical conditions, including if you:

- have nicotinamide adenine dinucleotide (NADH) reductase deficiency. People with NADH reductase deficiency have a higher risk for methemoglobinemia if they take ARAKODA.
- have or have had mental health problems.
- are pregnant or plan to become pregnant. ARAKODA can harm an unborn baby who has G6PD deficiency.
  - You should not become pregnant during treatment with ARAKODA.
  - Females who are able to become pregnant should use effective birth control (contraception) during treatment with ARAKODA. Talk with your healthcare provider about birth control methods that may be right for you.
  - Your healthcare provider may suggest you take a pregnancy test before you start taking ARAKODA. Tell your healthcare provider right away if you become pregnant or think you might be pregnant during treatment with ARAKODA.
- are breastfeeding or plan to breastfeed. It is not known if ARAKODA passes into breast milk. See “Do not take ARAKODA if you:”
  - Your healthcare provider should check your child for G6PD deficiency before you start breastfeeding.
  - If you know your child has G6PD deficiency, do not breastfeed during treatment with ARAKODA and for 3 months after your last dose of ARAKODA.

Tell your healthcare provider about all the medicines you take, including prescription and over-the-counter medicines, vitamins, and herbal supplements. ARAKODA and other medicines may affect each other causing side effects.

How should I take ARAKODA?

- Take ARAKODA exactly as your healthcare provider tells you to take it.
- ARAKODA is given as 2 tablets that you will take together as a single dose. Each ARAKODA tablet has 100 mg of tafenoquine.
- You will start taking ARAKODA 3 days before you travel to a malaria area.
  - Take 2 tablets, 1 time each day for 3 days.
- You will continue to take ARAKODA while you are in the malaria area.
  - Take 2 tablets, 1 time each week.
  - Start taking this dose of ARAKODA 7 days after the last dose of ARAKODA that you took before your travel to the malaria area.
- You will take your last dose of ARAKODA after you leave the malaria area.
  - Take 2 tablets.
  - Take this dose of ARAKODA 7 days after the last dose of ARAKODA that you took while you were in the malaria area.
- Take ARAKODA tablets whole. Do not break, crush, or chew the tablets before swallowing.
- Take ARAKODA with food.
- It is important that you take the full course of treatment with ARAKODA. Do not stop taking ARAKODA without first talking to your healthcare provider because the medicine may not work as well to prevent malaria.
- If you miss 1 or 2 daily doses of ARAKODA before your travel to the malaria area:
  - 1 daily dose: take 2 tablets (missed dose), and then continue to take your daily dose of ARAKODA until you have taken a total of 3 daily doses before your travel to the malaria area. Start taking your weekly doses or ARAKODA 1 week after your last daily dose.
  - 2 daily doses: take 2 tablets (missed dose), 1 time each day for 2 days in a row (consecutive days) so that you have taken a total of 3 daily doses before your travel to the malaria area. Start taking your weekly doses of ARAKODA 1 week after your last daily dose.
- If you miss any weekly doses of ARAKODA while you are in the malaria area:
  - 1 weekly dose: take 2 tablets, 1 time on any day up to the time of your next scheduled weekly dose.
  - 2 weekly doses: take 2 tablets, 1 time on any day before your next scheduled weekly dose.
  - 3 or more weekly doses: take 2 tablets, 1 time each day for 2 days up to the time of your next scheduled weekly dose.
- If you miss taking your last dose of ARAKODA 7 days after the last dose of ARAKODA you took while you were in the malaria area, take this last dose of ARAKODA as soon as you remember.

What are the possible side effects of ARAKODA?

ARAKODA may cause serious side effects, including:

- See “What is the most important information I should know about ARAKODA?”
- Allergic (hypersensitivity) reactions. See “Do not take ARAKODA if you:”
  Allergic reactions can happen after you take ARAKODA. Signs and symptoms of an allergic reaction may not happen right away (delayed reaction). Get medical help right away if you have any signs or symptoms of an allergic reaction including:
  - swelling of the face, lips, tongue or throat
  - itching
  - trouble breathing or wheezing
  - vomiting
  - fainting and feeling lightheaded
  - rash
  - hives

The most common side effects of ARAKODA include: diarrhea, headache, back pain, nausea, vomiting, dizziness, increased liver enzyme levels in your blood, motion sickness, insomnia, depression, abnormal dreams and anxiety.

Other side effects of ARAKODA include eye problems. Some people who take ARAKODA can have a problem with the cornea of the eye called vortex keratopathy. This problem can be seen during an eye exam. Vortex keratopathy does not cause vision problems and will usually go away after you stop taking ARAKODA.

These are not all the possible side effects of ARAKODA.

Call your doctor for medical advice about side effects. You may report side effects to FDA at 1-800-FDA-1088.

You may also report side effects to Sixty Degrees Pharmaceuticals, LLC at 1-888-834-0225.

How should I store ARAKODA?

- Store ARAKODA at room temperature between 68°F to 77°F (20°C to 25°C).
- Protect tablets from moisture.

Keep ARAKODA and all medicines out of the reach of children.

General information about the safe and effective use of ARAKODA.

Medicines are sometimes prescribed for purposes other than those listed in a Medication Guide. Do not use ARAKODA for a condition for which it was not prescribed. Do not give ARAKODA to other people, even if they have the same symptoms that you have. It may harm them.

You can ask your pharmacist or healthcare provider for information about ARAKODA that is written for health professionals.

What are the ingredients in ARAKODA?

Active ingredient: tafenoquine succinate

Inactive ingredients: microcrystalline cellulose, mannitol, and magnesium stearate. The tablet film-coating contains the following inactive ingredients: hypromellose, iron oxide red, titanium dioxide, and macrogol/polyethylene glycol.

Manufactured for:

Sixty Degrees Pharmaceuticals, LLC

Washington, DC 20036

For more information, go to https://60degreespharma.com or call 1-888-834-0225.

This Medication Guide has been approved by the U.S. Food and Drug Administration

Issued: August 2018

PRINCIPAL DISPLAY PANEL - Carton Label

Rx only

NDC: 71475-257-01

KEEP OUT OF REACH OF CHILDREN

ATTENTION: Dispense the enclosed
Medication Guide to each patient

Arakoda®
(tafenoquine) tablets,
for oral use

100 mg

16 (2 x 8)
Unit Dose Tablets

Sixty
Degrees
Pharma

Each tablet contains 100 mg tafenoquine (equivalent to 125.5 mg
tafenoquine succinate). Store below 30°C (86°F).

Protect from moisture. Dispense only in the original carton.

See Prescribing Information for Dosage and Administration
information.

Two blister packs are contained in each carton. Each
blister pack contains eight 100 mg tablets of
Arakoda® (tafenoquine), for oral use.

Manufactured for:
60 Degrees Pharmaceuticals, Inc.
1025 Connecticut Ave., NW, Suite 1000
Washington DC 20036

Country of Origin: India

Sixty
Degrees
Pharma

Arakoda®
(tafenoquine) tablets,
for oral use

Principal Display Panel - Inner Carton Label

Rx only

NDC: 71475-257-01

KEEP OUT OF REACH OF CHILDREN

ATTENTION: Dispense the enclosed
Medication Guide to each patient

Arakoda®
(tafenoquine) tablets,
for oral use

100 mg

16 (2 x 8)
Unit Dose Tablets

Sixty
Degrees
Pharma

Arakoda®
(tafenoquine) tablets,
for oral use

100 mg

Principal Display Panel - Blister Label

CODE: MP/DRUGS/25/10/92

NDC: 71475-257-01

21541667

EM 15572

Sixty
Degrees
Pharma

Arakoda®
(tafenoquine) tablets,
for oral use

100 mg

Exp:
Lot:

Principal Display Panel - Bottle Label

Rx only

NDC: 71475-257-02

KEEP OUT OF REACH
OF CHILDREN

ATTENTION: Dispense the attached
Medication Guide to each patient

Arakoda®
(tafenoquine) tablets,
for oral use

100 mg

8 Tablets

Sixty
Degrees
Pharma

Each tablet contains 100 mg
tafenoquine (equivalent to 125.5 mg
tafenoquine succinate). Store below
30ºC (86ºF).

Protect from moisture.

See Prescribing Information for Dosage
and Administration information.

Manufactured for:
60 Degrees Pharmaceuticals, Inc.
1025 Connecticut Ave., NW, Suite 1000
Washington DC 20036

Country of Origin: India